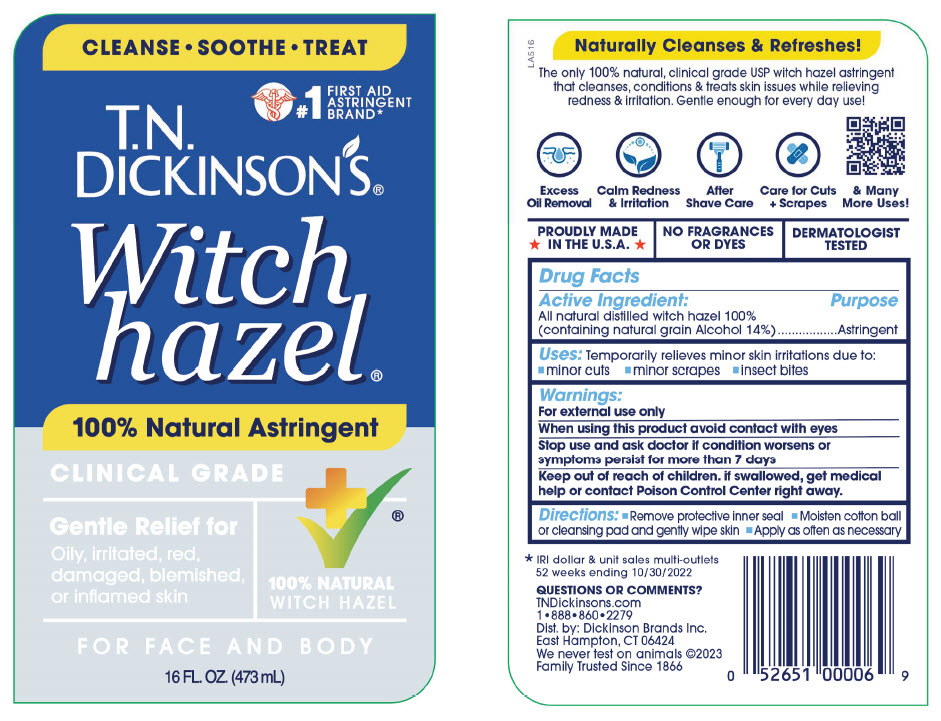 DRUG LABEL: TN Dickinsons Witch Hazel Astringent
NDC: 52651-001 | Form: LIQUID
Manufacturer: Dickinson Brands Inc.
Category: otc | Type: HUMAN OTC DRUG LABEL
Date: 20241125

ACTIVE INGREDIENTS: WITCH HAZEL 86 g/100 mL
INACTIVE INGREDIENTS: ALCOHOL

Drug Facts

Active Ingredient:
All Natural Witch Hazel 100% (containing Alcohol 14%)

Purpose

Astringent

Uses:

Temporarily relieves minor skin irritations due to:

- minor cuts
- minor scrapes
- insect bites

Warnings:

For external use only

When using this product avoid contact with eyes

Stop use and ask doctor if condition worsens or
symptoms persist for more than 7 days

Keep out of reach of children. If swallowed, get medical
help or contact Poison Control Center right away.

Directions:

- Remove protective inner seal
- Moisten cotton ball or cleansing pad and gently wipe skin
- Apply as often as necessary

Questions or Comments?
Call toll free: 1-888-860-2279
Dist. by: Dickinson Brands Inc.
East Hampton, CT 06424
MADE IN THE U.S.A.
www.tndickinsons.com
No animal testing

PRINCIPAL DISPLAY PANEL - 473 mL Bottle Label

CLEANSE•SOOTHE•TREAT

#1
FIRST AID
ASTRINGENT
BRAND*

T.N.
DICKINSON'S®

Witch
hazel®

100% Natural Astringent

CLINICAL GRADE

Gentle Relief for
Oily, irritated, red,
damaged, blemished,
or inflamed skin

100% NATURAL
WITCH HAZEL

FOR FACE AND BODY

16 FL. OZ. (473 mL)